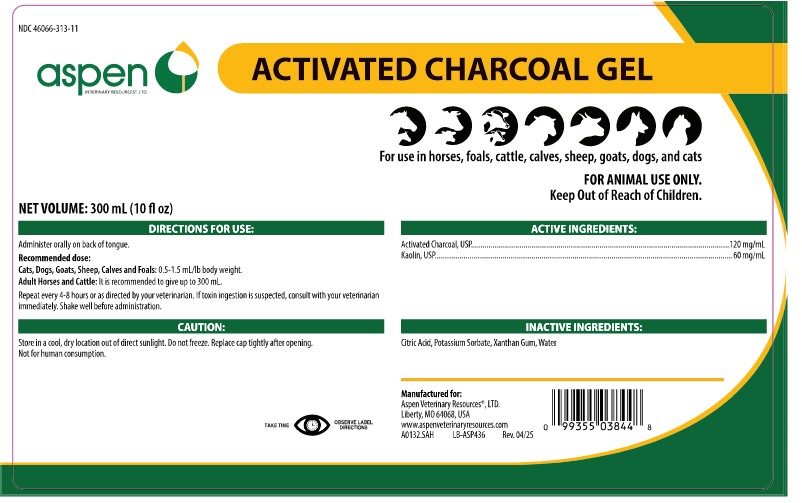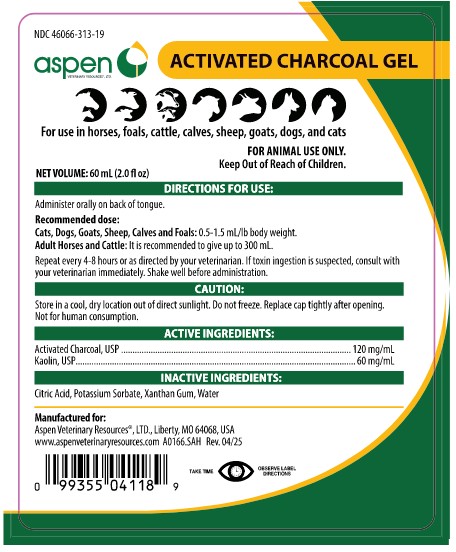 DRUG LABEL: Activated Charcoal Gel
NDC: 46066-313 | Form: GEL
Manufacturer: Aspen Veterinary Resources, Ltd.
Category: animal | Type: OTC ANIMAL DRUG LABEL
Date: 20250613

ACTIVE INGREDIENTS: ACTIVATED CHARCOAL 55 [arb'U]/1 mL
INACTIVE INGREDIENTS: KAOLIN; POTASSIUM SORBATE; CITRIC ACID; XANTHAN GUM; WATER

Activated Charcoal Gel

VETERINARY INDICATIONS

INDICATION:

Activated Charcoal Gel is a veterinary aid designed to assist in the absorption of toxins. This gel formulation is used in emergency situations involving suspected toxicosis in animals such as cattle, horses, goats, dogs, and cats.

In all cases of suspected poisonings, consult your veterinarian for complete diagnosis and specific treatment.

DOSAGE AND ADMINISTRATION:

Administer orally on the back of the tongue.

Cats, Dogs, Goats, Sheep, Calves and Foals: 0.5-1.5 mL/lb body weight.

Adult Horses and Cattle: It is recommended to give up to 300 mL.

Repeat every 4-8 hours or as directed by your veterinarian. If toxin ingestion is suspected, consult with your veterinarian immediately. Shake well before administration.

PRECAUTIONS

Activated charcoal gel may not be effective against poisoning by mercury, other heavy metals, or inorganic arsenic.

STORAGE AND HANDLING

Store in a cool, dry location out of direct sunlight.

Do not freeze.

Replace cap tightly after opening.

Not for human consumption.

Keep out of reach of children.

HOW SUPPLIED

Activated Charcoal Gel is available in 300cc and 60cc multi-dose syringes for flexible and precise dosing.

Aspen Veterinary Resources, Ltd.
Liberty, MO 64068, USA

Rev. 06/25

PRINCIPAL DISPLAY PANEL - 300 mL Syringe Label

NDC 46066-313-11

Aspen Veterinary Resources Ltd.

Activated Charcoal Gel

INDICATION:

For oral administration as an aid in treating poisoning by most organic chemicals in large and small animals.

Net Volume: 300 mL (10 fl oz)

PRINCIPAL DISPLAY PANEL - 60 mL Syringe Label

NDC 46066-313-19

Aspen Veterinary Resources Ltd.

Activated Charcoal Gel

INDICATION:

For oral administration as an aid in treating poisoning by most organic chemicals in large and small animals.

Net Volume: 60 mL (2 fl oz)